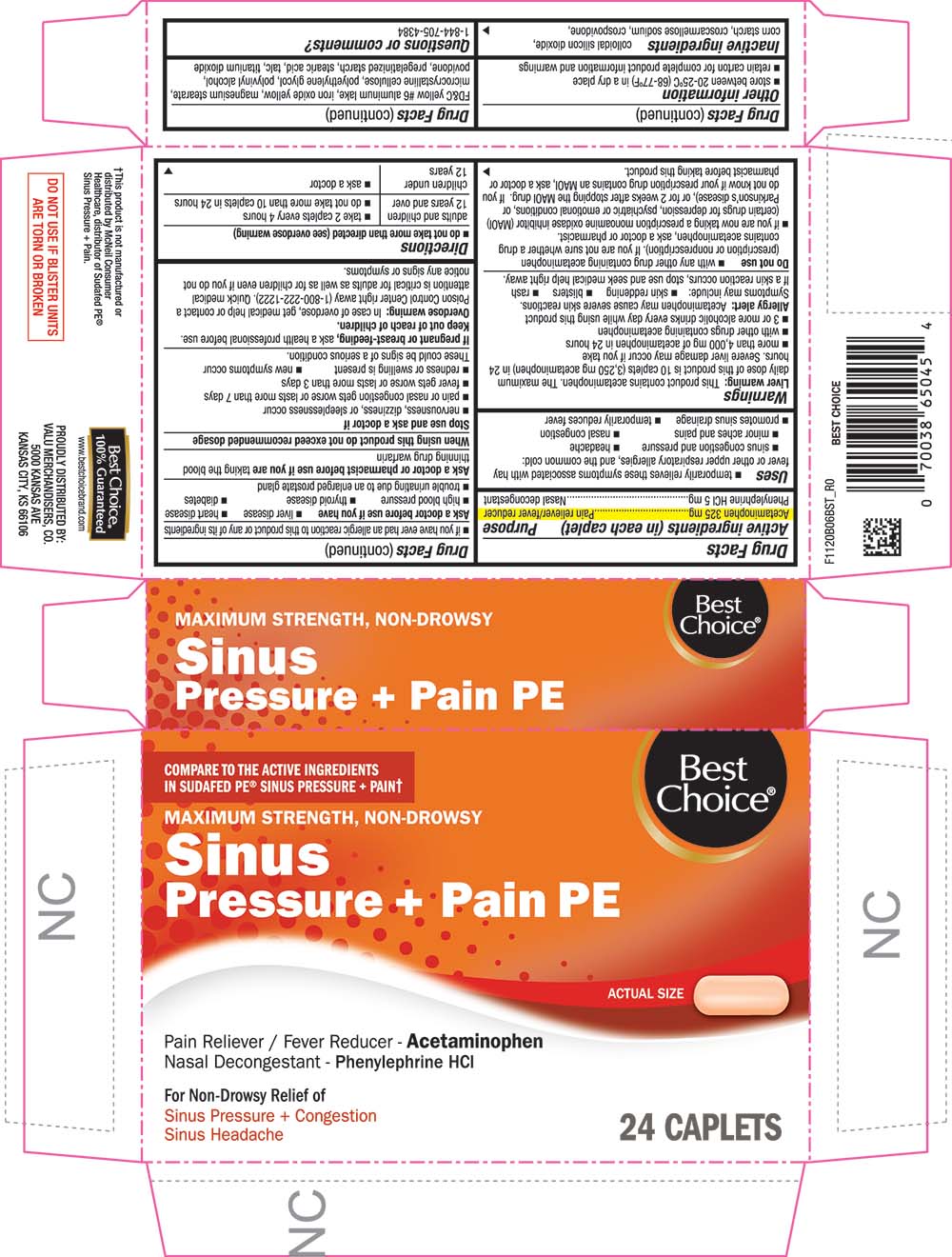 DRUG LABEL: Sinus Pressure plus Pain PE
NDC: 63941-220 | Form: TABLET, COATED
Manufacturer: VALU MERCHANDISERS COMPANY
Category: otc | Type: HUMAN OTC DRUG LABEL
Date: 20251211

ACTIVE INGREDIENTS: ACETAMINOPHEN 325 mg/1 1; PHENYLEPHRINE HYDROCHLORIDE 5 mg/1 1
INACTIVE INGREDIENTS: SILICON DIOXIDE; CROSCARMELLOSE SODIUM; CROSPOVIDONE; FD&C YELLOW NO. 6; ALUMINUM OXIDE; FERRIC OXIDE YELLOW; MAGNESIUM STEARATE; CELLULOSE, MICROCRYSTALLINE; POLYETHYLENE GLYCOL, UNSPECIFIED; POLYVINYL ALCOHOL, UNSPECIFIED; POVIDONE, UNSPECIFIED; STARCH, CORN; STEARIC ACID; TALC; TITANIUM DIOXIDE

1120B-BST-2021-1117

Drug Facts

ACTIVE INGREDIENT

Active ingredients (in each caplet) | Purpose
Acetaminophen 325 mg | Pain reliever/fever reducer
Phenylephrine HCl 5 mg | Nasal decongestant

Uses

- temporarily relieves these symptoms associated with hay fever or other upper respiratory allergies, and the common cold:
  - sinus congestion and pressure
  - headache
  - minor aches and pains
  - nasal congestion
- promotes sinus drainage
- temporarily reduces fever

Warnings

Liver warning

This product contains acetaminophen. The maximum daily dose of this product is 10 caplets (3,250 mg acetaminophen) in 24 hours. Severe liver damage may occur if you take

- more than 4,000 mg of acetaminophen in 24 hours
- with other drugs containing acetaminophen
- 3 or more alcoholic drinks every day while using this product

Allergy alert

Acetaminophen may cause severe skin reactions. Symptoms may include:

- skin reddening
- blisters
- rash

If a skin reaction occurs, stop use and seek medical help right away.

Do not use

- with any other drug containing acetaminophen (prescription or nonprescription). If you are not sure whether a drug contains acetaminophen, ask a doctor or pharmacist.
- if you are now taking a prescription monoamine oxidase inhibitor (MAOI) (certain drugs for depression, psychiatric or emotional conditions, or Parkinson's disease), or for 2 weeks after stopping the MAOI drug. If you do not know if your prescription drug contains an MAOI, ask a doctor or pharmacist before taking this product.
- if you have ever had an allergic reaction to this product or any of its ingredients

Ask a doctor before use if you have

- liver disease
- heart disease
- high blood pressure
- thyroid disease
- diabetes
- trouble urinating due to an enlarged prostate gland

Ask a doctor or pharmacist before use if you are taking the blood thinning drug warfarin

When using this product do not exceed recommended dosage

Stop use and ask a doctor if

- nervousness, dizziness, or sleeplessness occur
- pain or nasal congestion gets worse or lasts more than 7 days
- fever gets worse or lasts more than 3 days
- redness or swelling is present
- new symptoms occur

These could be signs of a serious condition.

PREGNANCY OR BREAST FEEDING

If pregnant or breast-feeding, ask a health professional before use.

Overdose warning

In case of overdose, get medical help or contact a Poison Control Center right away (1-800-222-1222). Quick medical attention is critical for adults as well as for children even if you do not notice any signs or symptoms.

Directions

- do not take more than directed (see overdose warning)

adults and children 12 years and over | - take 2 caplets every 4 hours - do not take more than 10 caplets in 24 hours
children under 12 years | - ask a doctor

Other information

- store between 20-25ºC (68-77ºF) in a dry place
- retain carton for complete product information and warnings

Inactive ingredients

colloidal silicon dioxide, corn starch, croscarmellose sodium, crospovidone, FD&C yellow #6 aluminum lake, iron oxide yellow, magnesium stearate, microcrystalline cellulose, polyethylene glycol, polyvinyl alcohol, povidone, pregelatinized starch, stearic acid, talc, titanium dioxide

Questions or comments?

1-844-705-4384

PRINCIPAL DISPLAY PANEL

COMPARE TO THE ACTIVE INGREDIENTS IN SUDAFED® SINUS PRESSURE + PAIN†

MAXIMUM STRENGTH, NON-DROWSY

Sinus Pressure + Pain PE

ACTUAL SIZE

Pain Reliever / Fever Reducer - Acetaminophen

Nasal Decongestant - Phenylephrine HCl

For Non-Drowsy Relief of

Sinus Pressure + Congestion

Sinus Headache

24 CAPLETS